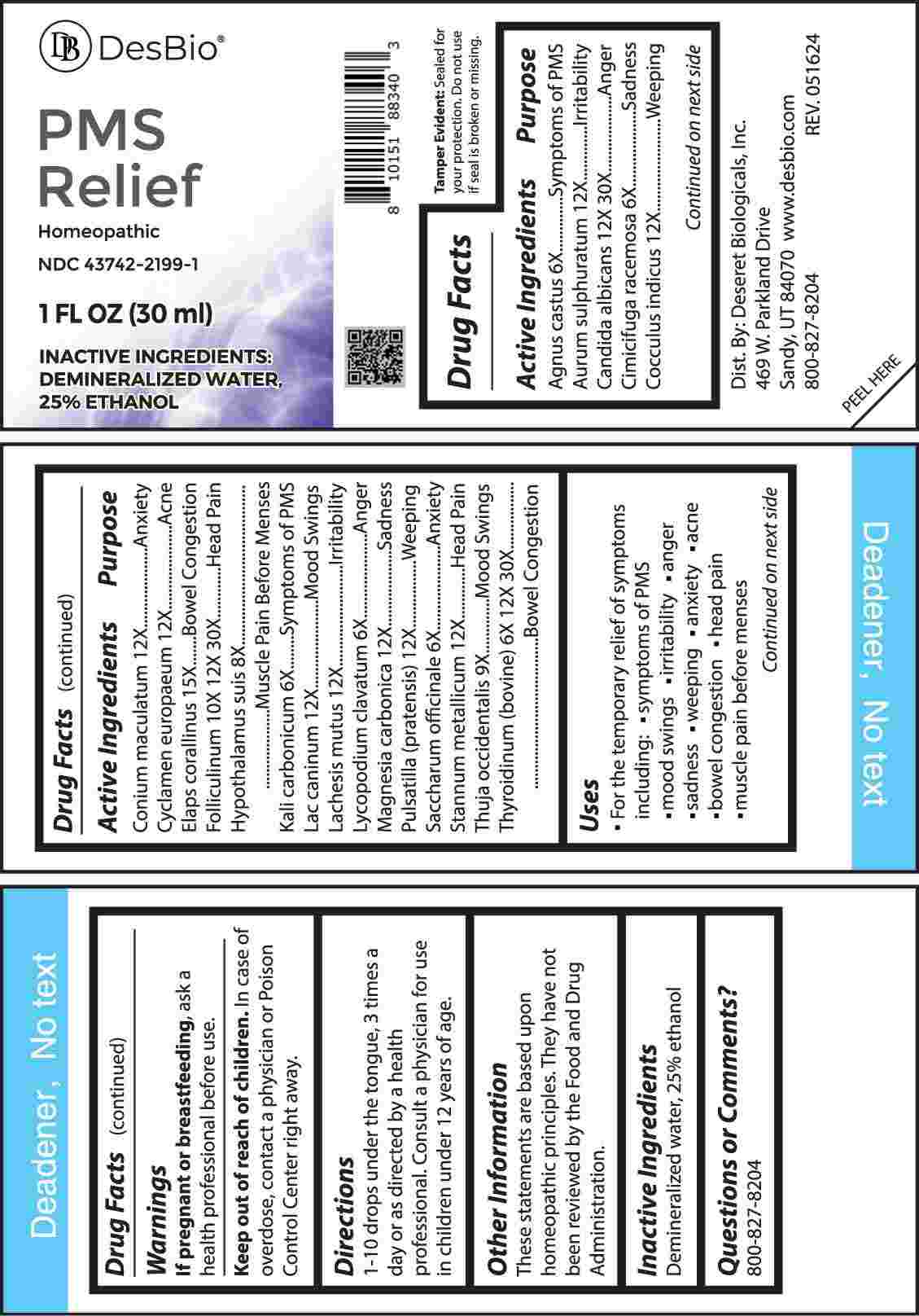 DRUG LABEL: PMS Relief
NDC: 43742-2199 | Form: LIQUID
Manufacturer: Deseret Biologicals, Inc.
Category: homeopathic | Type: HUMAN OTC DRUG LABEL
Date: 20240923

ACTIVE INGREDIENTS: CHASTE TREE FRUIT 6 [hp_X]/1 mL; GOLD MONOSULFIDE 12 [hp_X]/1 mL; CANDIDA ALBICANS 12 [hp_X]/1 mL; BLACK COHOSH 6 [hp_X]/1 mL; ANAMIRTA COCCULUS SEED 12 [hp_X]/1 mL; CONIUM MACULATUM FLOWERING TOP 12 [hp_X]/1 mL; CYCLAMEN PURPURASCENS TUBER 12 [hp_X]/1 mL; MICRURUS CORALLINUS VENOM 15 [hp_X]/1 mL; ESTRONE 10 [hp_X]/1 mL; SUS SCROFA HYPOTHALAMUS 8 [hp_X]/1 mL; POTASSIUM CARBONATE 6 [hp_X]/1 mL; CANIS LUPUS FAMILIARIS MILK 12 [hp_X]/1 mL; LACHESIS MUTA VENOM 12 [hp_X]/1 mL; LYCOPODIUM CLAVATUM SPORE 6 [hp_X]/1 mL; MAGNESIUM CARBONATE 12 [hp_X]/1 mL; PULSATILLA PRATENSIS WHOLE 12 [hp_X]/1 mL; SUCROSE 6 [hp_X]/1 mL; TIN 12 [hp_X]/1 mL; THUJA OCCIDENTALIS LEAFY TWIG 9 [hp_X]/1 mL; THYROID, BOVINE 6 [hp_X]/1 mL
INACTIVE INGREDIENTS: WATER; ALCOHOL

DRUG FACTS:

ACTIVE INGREDIENTS:

Agnus Castus 6X, Aurum Sulphuratum 12X, Candida Albicans 12X, 30X, Cimicifuga Racemosa 6X, Cocculus Indicus 12X, Conium Maculatum 12X, Cyclamen Europaeum 12X, Elaps Corallinus 15X, Folliculinum 10X, 12X, 30X, Hypothalamus Suis 8X, Kali Carbonicum 6X, Lac Caninum 12X, Lachesis Mutus 12X, Lycopodium Clavatum 6X, Magnesia Carbonica 12X, Pulsatilla (Pratensis) 12X, Saccharum Officinale 6X, Stannum Metallicum 12X, Thuja Occidentalis 9X, Thyroidinum (Bovine) 6X, 12X, 30X.

PURPOSE:

Agnus Castus – Symptoms of PMS, Aurum Sulphuratum - Irritability, Candida Albicans - Anger, Cimicifuga Racemosa - Sadness, Cocculus Indicus - Weeping, Conium Maculatum - Anxiety, Cyclamen Europaeum - Acne, Elaps Corallinus – Bowel Congestion, Folliculinum – Head Pain, Hypothalamus Suis – Muscle Pain Before Menses, Kali Carbonicum – Symptoms of PMS, Lac Caninum – Mood Swings, Lachesis Mutus - Irritability, Lycopodium Clavatum - Anger, Magnesia Carbonica - Sadness, Pulsatilla (Pratensis) - Weeping, Saccharum Officinale - Anxiety, Stannum Metallicum – Head Pain, Thuja Occidentalis – Mood Swings, Thyroidinum (Bovine) – Bowel Congestion

USES:

• For the temporary relief of symptoms including:

• symptoms of PMS • mood swings • irritability • anger • sadness • weeping

• anxiety • acne • bowel congestion • head pain • muscle pain before menses

These statements are based upon homeopathic principles. They have not been reviewed by the Food and Drug Administration.

WARNINGS:

If pregnant or breast-feeding, ask a health professional before use.

Keep out of reach of children. In case of overdose, contact a physician or Poison Control Center right away.

Tamper Evident: Sealed for your protection. Do not use if seal is broken or missing.

KEEP OUT OF REACH OF CHILDREN:

In case of overdose, contact a physician or Poison Control Center right away.

DIRECTIONS:

1-10 drops under the tongue, 3 times a day or as directed by a health professional. Consult a physician for use in children under 12 years of age.

INACTIVE INGREDIENTS:

Demineralized water, 25% ethanol

QUESTIONS:

Dist. By: Deseret Biologicals, Inc.

469 W. Parkland Drive

Sandy, UT 84070

www.desbio.com

800-827-8204

PACKAGE LABEL DISPLAY:

DesBio

PMS Relief

Homeopathic

NDC 43742-2199-1

1 FL OZ (30 ml)